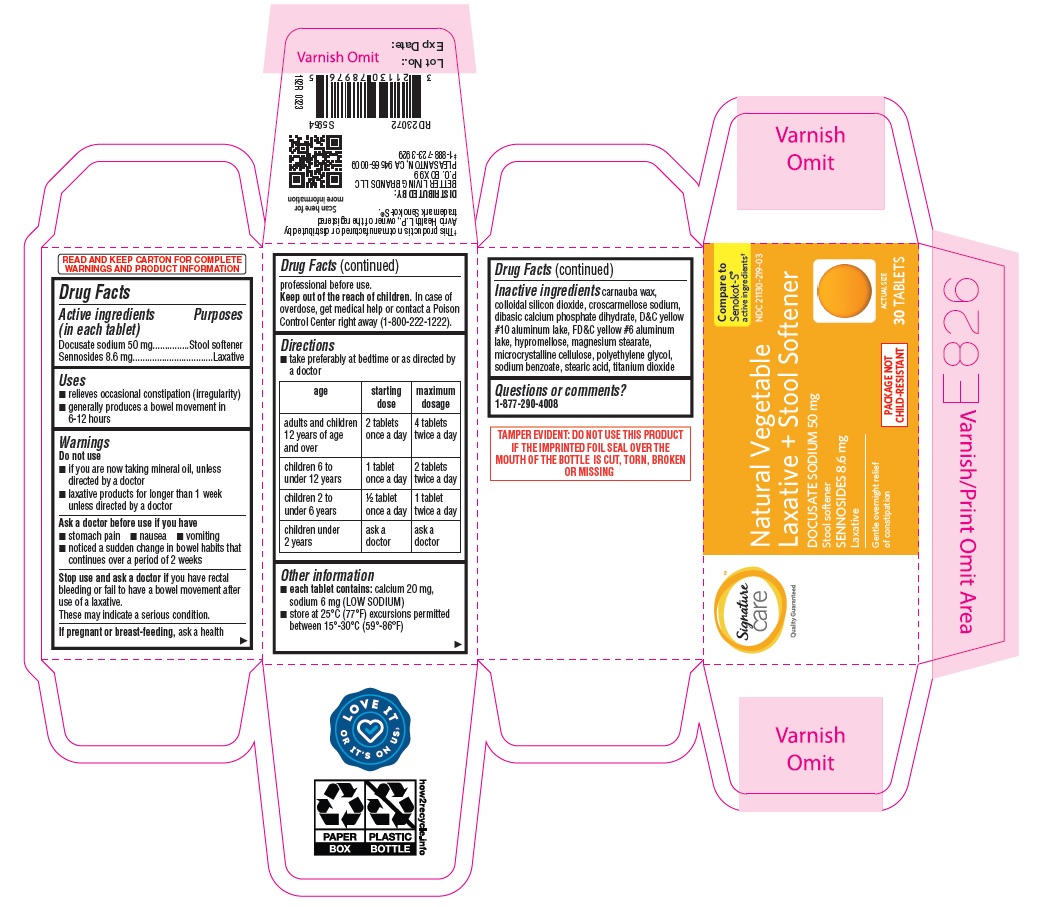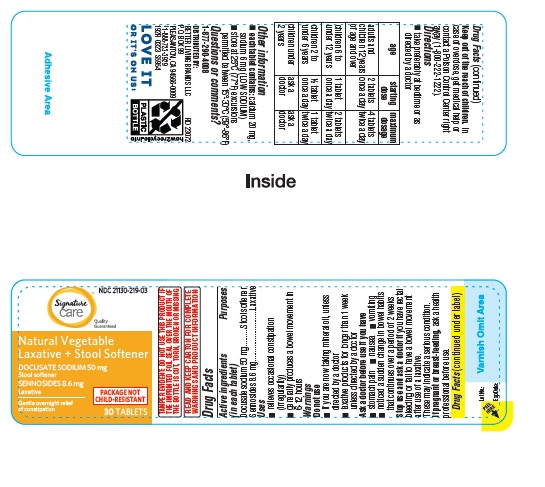 DRUG LABEL: Natural Vegetable Laxative and Stool Softener
NDC: 21130-219 | Form: TABLET
Manufacturer: BETTER LIVING BRANDS LLC.
Category: otc | Type: HUMAN OTC DRUG LABEL
Date: 20240925

ACTIVE INGREDIENTS: DOCUSATE SODIUM 50 mg/1 1; SENNOSIDES 8.6 mg/1 1
INACTIVE INGREDIENTS: CARNAUBA WAX; SILICON DIOXIDE; D&C YELLOW NO. 10 ALUMINUM LAKE; FD&C YELLOW NO. 6; MAGNESIUM STEARATE; HYPROMELLOSE, UNSPECIFIED; DIBASIC CALCIUM PHOSPHATE DIHYDRATE; MICROCRYSTALLINE CELLULOSE; SODIUM BENZOATE; STEARIC ACID; TITANIUM DIOXIDE; POLYETHYLENE GLYCOL, UNSPECIFIED; CROSCARMELLOSE SODIUM

Albertsons Sennosides 8.6 mg Tablets

Active ingredients (in each tablet)

Docusate sodium 50 mg

Sennosides 8.6 mg

Purposes

Stool softener

Laxative

Uses

- relieves occasional constipation (irregularity)
- generally produces a bowel movement in 6-12 hours

Warnings

Do not use

- if you are now taking mineral oil, unless directed by a doctor
- laxative products for longer than 1 week unless directed by a doctor

Ask a doctor before use if you have

- stomach pain
- nausea
- vomiting
- noticed a sudden change in bowel habits that continues over a period of 2 weeks

Stop use and ask a doctor if you have rectal bleeding or fail to have a bowel movement after use of a laxative. These may indicate a serious condition

PREGNANCY OR BREAST FEEDING

If pregnant or breast-feeding, ask a health professional before use.

KEEP OUT OF REACH OF CHILDREN

Keep out of the reach of children. In case of overdose, get medical help or contact a Poison Control Center right away (1-800-222-1222).

Directions

- take preferably at bedtime or as directed by a doctor

age | starting dose | maximum dosage
adults and children 12 years of age and over | 2 tablets once a day | 4 tablets twice a day
children 6 to under 12; years | 1 tablet once a day | 2 tablets twice a day
children 2 to under 6; years | ½ tablet once a day | 1 tablet twice a day
children under 2 years | ask a doctor | ask a doctor

Other information

- each tablet contains: calcium 20 mg, sodium 6 mg (LOW SODIUM)
- store at 25°C (77°F) excursions permitted between 15°-30°C (59°-86°F)

INACTIVE INGREDIENT

Inactive ingredients carnauba wax, colloidal silicon dioxide, croscarmellose sodium, dibasic calcium phosphate dihydrate, D&C yellow #10 aluminum lake, FD&C yellow #6 aluminum lake, hypromellose, magnesium stearate, microcrystalline cellulose, polyethylene glycol, sodium benzoate, stearic acid, titanium dioxide

Questions or comments? Call 1-877-290-4008